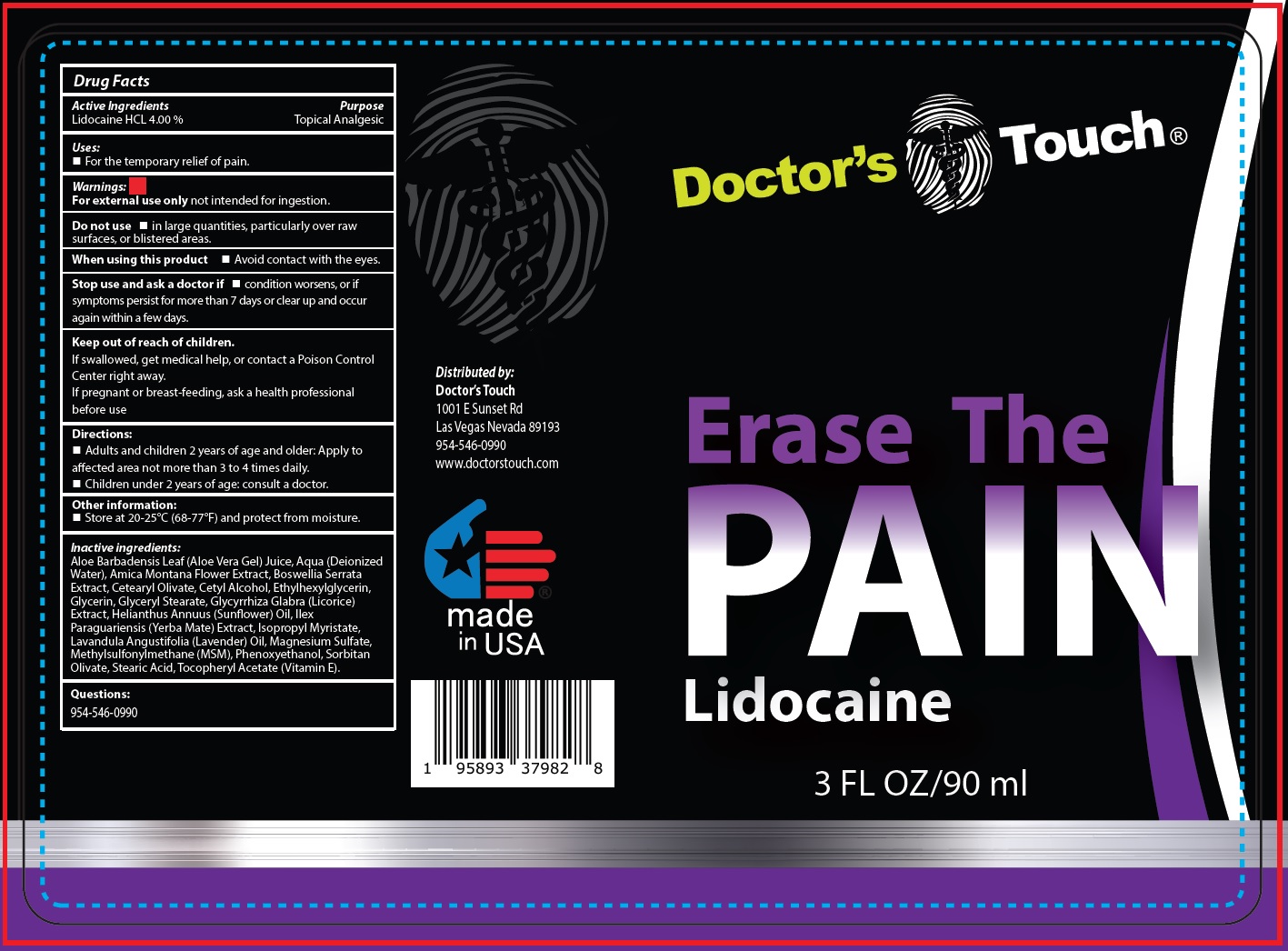 DRUG LABEL: DOCTORS TOUCH Erase The Pain Lidocaine
NDC: 80045-400 | Form: LIQUID
Manufacturer: DOCTOR'S CHOICE MEDICAL, LLC
Category: otc | Type: HUMAN OTC DRUG LABEL
Date: 20231106

ACTIVE INGREDIENTS: LIDOCAINE HYDROCHLORIDE 40 mg/1 mL
INACTIVE INGREDIENTS: ALOE VERA LEAF; WATER; ARNICA MONTANA FLOWER; INDIAN FRANKINCENSE; CETEARYL OLIVATE; CETYL ALCOHOL; ETHYLHEXYLGLYCERIN; GLYCERIN; GLYCERYL MONOSTEARATE; GLYCYRRHIZA GLABRA; HELIANTHUS ANNUUS FLOWERING TOP; ILEX PARAGUARIENSIS LEAF; ISOPROPYL MYRISTATE; LAVENDER OIL; MAGNESIUM SULFATE, UNSPECIFIED FORM; DIMETHYL SULFONE; PHENOXYETHANOL; SORBITAN OLIVATE; STEARIC ACID; .ALPHA.-TOCOPHEROL ACETATE

DOCTOR'S TOUCH Erase The Pain - Lidocaine

Active Ingredients

Lidocaine HCL 4.00 %

Purpose

Topical Analgesic

Uses:

- For the temporary relief of pain.

Warnings:

not intended for ingestion. For external use only

Do not use

- in large quantities, particularly over raw surfaces, or blistered areas.

When using this product

- Avoid contact with the eyes.

Avoid contact with the eyes.

- condition worsens, or if symptoms persist for more than 7 days or clear up and occur again within a few days.

Keep out of reach of children.

If swallowed, get medical help, or contact a Poison Control Center right away.

If pregnant or breast-feeding,

ask a health professional before use

Directions:

- Adults and children 2 years of age and older: Apply to affected area not more than 3 to 4 times daily.
- Children under 2 years of age: consult a doctor.

Other information:

- Store at 20-25°C (68-77°F) and protect from moisture.

Inactive ingredients:

Aloe Barbadensis Leaf (Aloe Vera Gel) Juice, Aqua (Deionized Water), Amica Montana Flower Extract, Boswellia Serrata Extract, Cetearyl Olivate, Cetyl Alcohol, Ethylhexylglycerin, Glycerin, Glyceryl Stearate, Glycyrrhiza Glabra (Licorice) Extract, Helianthus Annuus (Sunflower) Oil, Ilex Paraguariensis (Yerba Mate) Extract, lsopropyl Myristate, Lavandula Angustifolia (Lavender) Oil, Magnesium Sulfate, Methylsulfonylmethane (MSM), Phenoxyethanol, Sorbitan Olivate, Stearic Acid, Tocopheryl Acetate (Vitamin E).

Questions:

954-546-0990